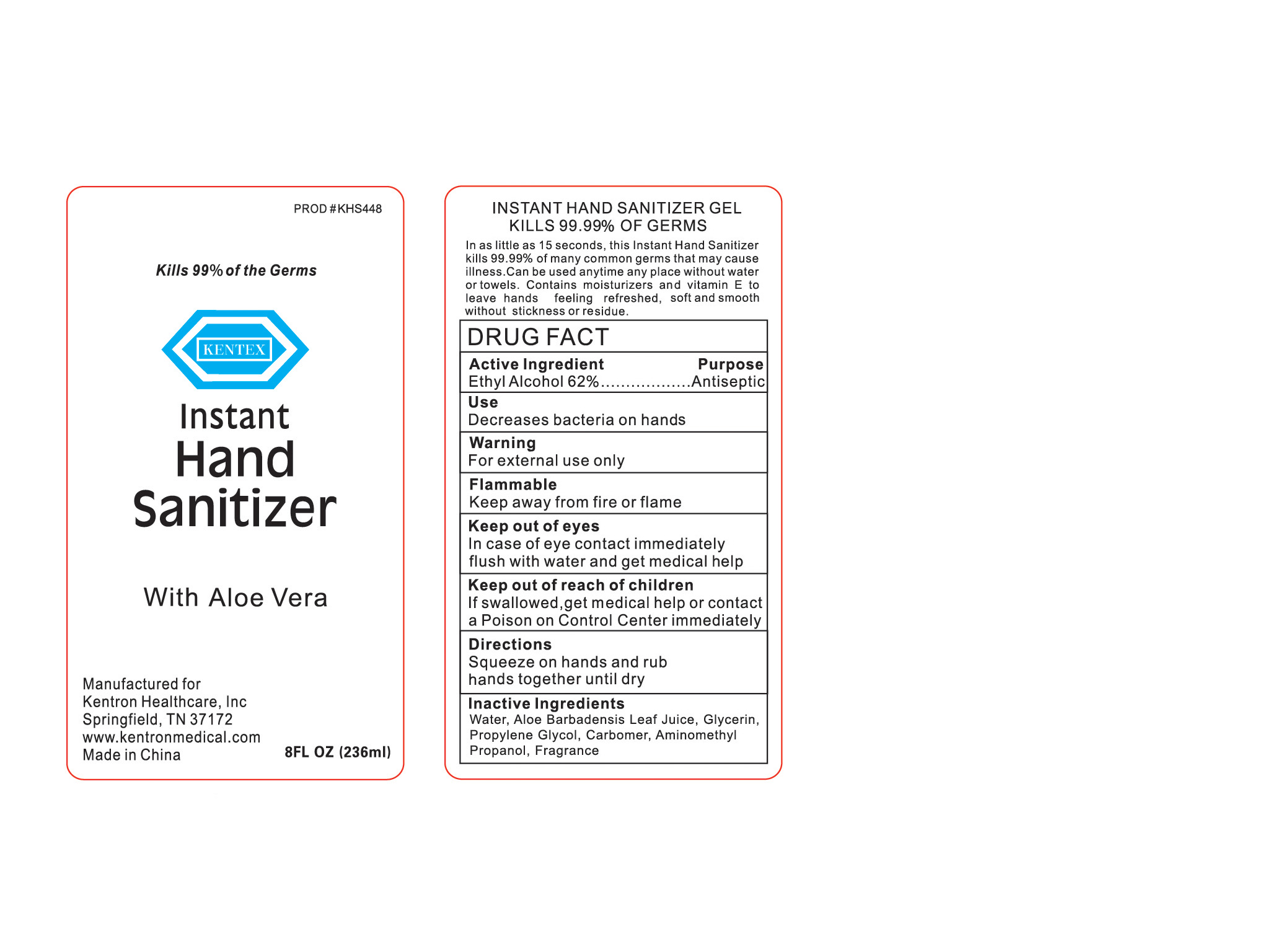 DRUG LABEL: Hand Sanitizer with Aloe Vera
NDC: 69556-001 | Form: GEL
Manufacturer: Kentron Healthcare, Inc.
Category: otc | Type: HUMAN OTC DRUG LABEL
Date: 20160217

ACTIVE INGREDIENTS: ALCOHOL 62 mL/100 mL
INACTIVE INGREDIENTS: WATER; ALOE VERA LEAF; GLYCERIN; PROPYLENE GLYCOL; CARBOMER INTERPOLYMER TYPE A (55000 CPS); AMINOMETHYL PROPANEDIOL

Active Ingredient
Ethyl Alcohol 62%

Purpose

Antiseptic

Warning

For external use only

Flammable

Keep away from fire or flame

Keep out of reach of children.

If swallowed, get medical help or contact a Poison Control Center immediately

Directions

Squeeze on hands and rub hands together until dry

Inactive Ingredients

Water, Aloe Barbadensis Leaf Juice, Glycerin, Propylene Glycol, Carbomer, Aminomethyl Propanol, Fragrance

Use

Decreases bacteria on the hands

OTHER SAFETY INFORMATION

Keep out of eyes

In case of eye contact immediately flush with water and get medical help